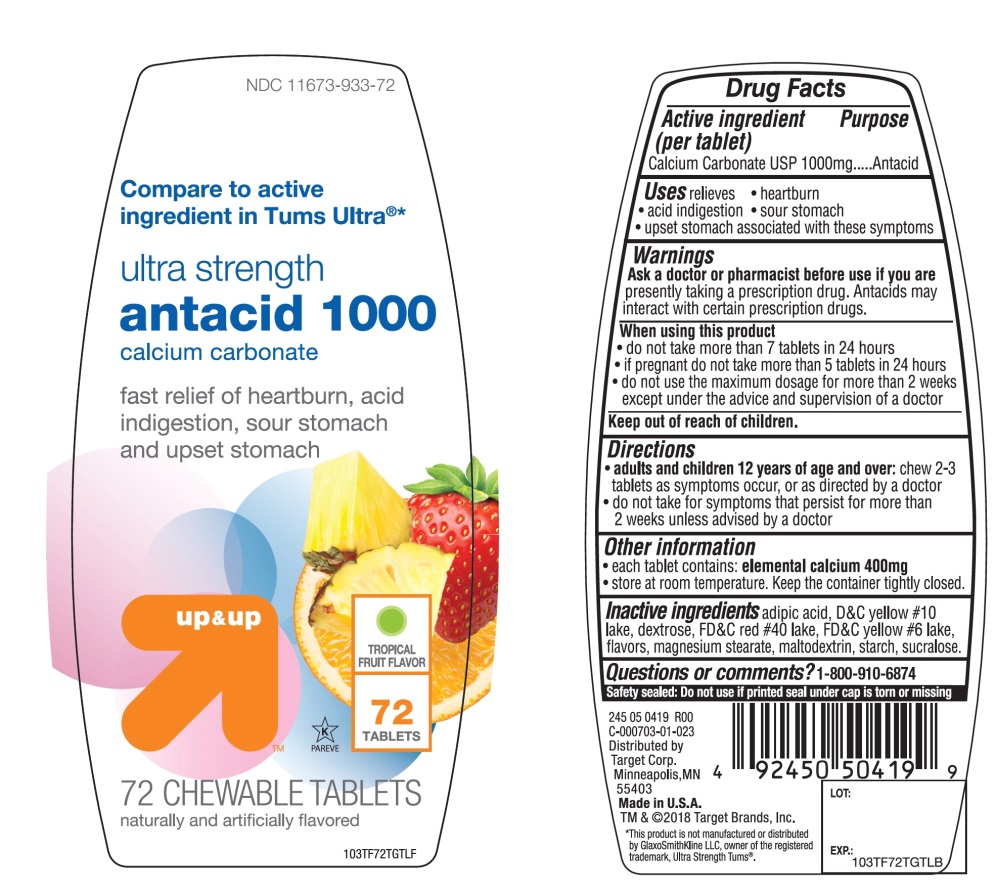 DRUG LABEL: ultra strength antacid
NDC: 11673-933 | Form: TABLET, CHEWABLE
Manufacturer: Target Corporation
Category: otc | Type: HUMAN OTC DRUG LABEL
Date: 20251104

ACTIVE INGREDIENTS: CALCIUM CARBONATE 1000 mg/1 1
INACTIVE INGREDIENTS: ADIPIC ACID; D&C YELLOW NO. 10; DEXTROSE, UNSPECIFIED FORM; FD&C RED NO. 40; FD&C YELLOW NO. 6; MAGNESIUM STEARATE; MALTODEXTRIN; STARCH, CORN; SUCRALOSE

up&up ultra strength antacid calcium carbonate Tropical Fruit 72 Chewable Tablets

Active ingredient (per tablet)

Calcium Carbonate USP 1000mg

Purpose

Antacid

Uses

relieves

- heartburn
- acid indigestion
- sour stomach
- upset stomach associated with these symptoms

Warnings

Ask a doctor or pharmacist before use if you arepresently taking a prescription drug. Antacids may interact with certain prescription drugs.

When using this product

- do not take more than 7 tablets in 24 hours
- if pregnant do not take more than 5 tablets in 24 hours
- do not use the maximum dosage for more than 2 weeks except under the advice and supervision of a doctor.

Directions

- adults and children 12 years of age and over:chew 2-3 tablets as symptoms occur, or as directed by a doctor
- do not take for symptoms that persist for more than 2 weeks unless advised by a doctor

Other information

- each tablet contains: elemental calcium 400mg
- store at room temperature. Keep the container tightly closed

Inactive ingredients

adipic acid, D&C yellow 10 lake, dextrose, FD&C red 40 lake, FD&C yellow 6 lake, flavors, magnesium stearate, maltodextrin, starch, sucralose

Questions?

1-800-910-6874

Safety sealed: Do not use if printed seal under cap is torn or missing

Package/Label Principal Display Panel

NDC 11673-933-72

Compare to active ingredient* Tums®Ultra

ultra strength

antacid 1000

calcium carbonate

fast relief of heartburn, acid indigestion ,sour stomach and upset stomach

Tropical Fruit Flavor

naturally and artificially flavored

72 CHEWABLE TABLETS

Gluten- Free

Distributed by Target Corp., Minneapolis, MN 55403

Made in U.S.A

TM & @2018 Target Brands Inc.

*This product is not manufactured or distributed by GlaxoSmithKline LLC, owner of the registered trademark, Ultra Strength Tums®.